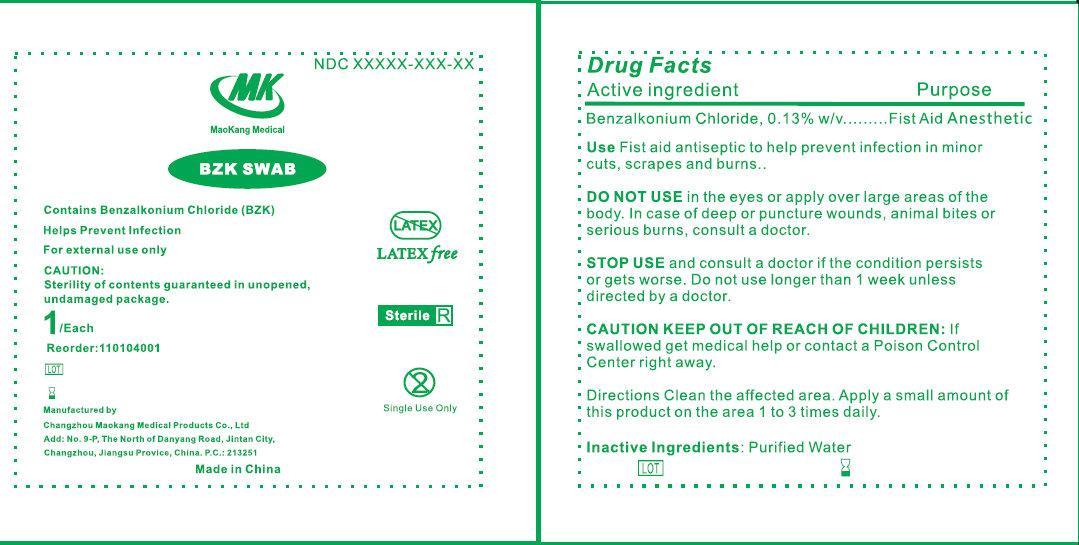 DRUG LABEL: MK BZK Swab Sterile
NDC: 59050-434 | Form: LIQUID
Manufacturer: Changzhou Maokang Medical Products Co., Ltd
Category: otc | Type: HUMAN OTC DRUG LABEL
Date: 20140305

ACTIVE INGREDIENTS: BENZALKONIUM CHLORIDE 1.3 mg/1 mL
INACTIVE INGREDIENTS: WATER

MK BZK Swab Sterile

Active ingredient

Benzalkonium Chloride, 0.13% w/w

Purpose

First Aid Anesthetic

Use

Fist aid antiseptic to help prevent infection in minor cuts, scrapes and burns.

WARNINGS

For external use only

DO NOT USE

- in the eyes or apply over large areas of the body.
- In case of deep or puncture wounds, animal bites or serious burns, consult a doctor.

STOP USE

and consult a doctor if the condition persists or gets worse. Do not use longer than 1 week unless directed by a doctor.

CAUTION KEEP OUT OF REACH OF CHILDREN:

If swallowed, get medical help or contact a Poison Control center right away.

Directions

Clean the affected area. Apply a small amount of this product on the area 1 to 3 times daily.

Inactive ingredients:

Purified Water